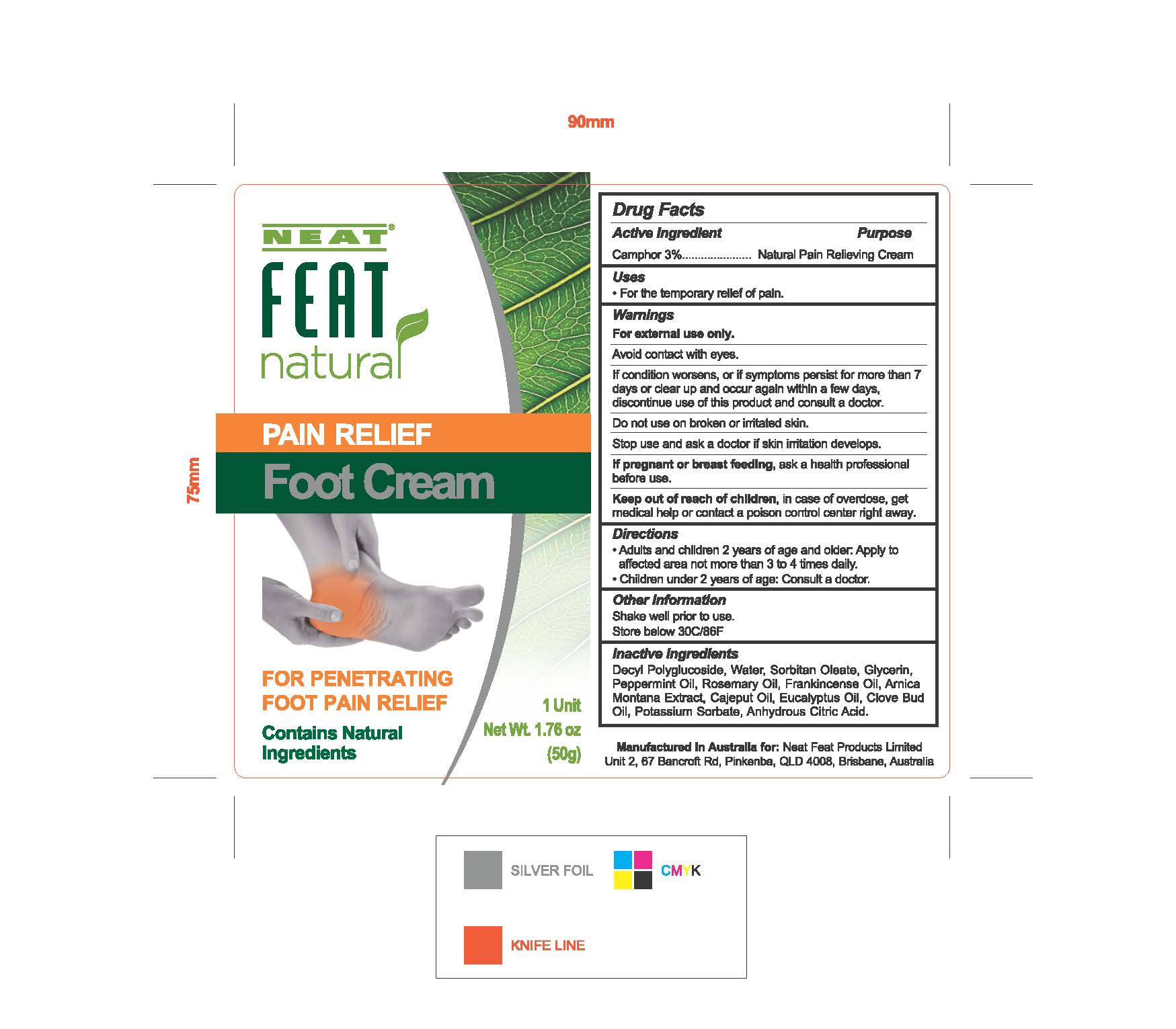 DRUG LABEL: Natural Pain Relief Foot Cream
NDC: 50017-033 | Form: CREAM
Manufacturer: Neat Feat Products Limited
Category: homeopathic | Type: HUMAN OTC DRUG LABEL
Date: 20250108

ACTIVE INGREDIENTS: CAMPHOR (NATURAL) 1.5 g/50 g
INACTIVE INGREDIENTS: ANHYDROUS CITRIC ACID; PEPPERMINT OIL; WATER; ARNICA MONTANA; CAJUPUT OIL; PEG-6 SORBITAN OLEATE; GLYCERIN; ROSEMARY OIL; EUCALYPTUS OIL; POTASSIUM SORBATE; DECYL GLUCOSIDE; FRANKINCENSE OIL; CLOVE OIL

Pain Relief Foot Cream

PACKAGE LABEL

50 g NDC: 50017-033-01

ACTIVE INGREDIENT

Camphor 3% .................... Natural Pain Relieving Cream

PURPOSE

For the temporary relief of pain

WARNINGS

For external use only.

Avoid con1act with eyes.

If condition worsens, or if symptoms persist for more than 7 days or clear up and occur again within a few days, discontinue use of this product and consult a doctor.

Do not use on broken or irritated skin.

Slop use and ask a doctor if skin irritation develops.

If pregnant or tnnt feeding, ask a health professional before use.

Keep out of reach of chlklren, in case of overdose, get medical help or contact a poison control center right away.

INDICATIONS AND USAGE

For the temporary relief of pain.

KEEP OUT OF REACH OF CHILDREN

Keep out of reach of childen, in case of overdose, get medical help or contact a poison control center right away.

DOSAGE AND ADMINISTRATION

Adults and chlldren 2 years of age and older: Apply to affected area not more than 3 to 4 times daily.
Children under 2 years of age: Consult a doclor.

OTHER SAFETY INFORMATION

Shake well prior to use.

Store below 30C/86F

INACTIVE INGREDIENT

Decyl Polyglucoside, Water, Sorbitan Oleate, Glycerin, Peppermint Oil, Rosemary Oil, Frankincense Oil, Amica Montana Extract, Cajeput Oil, Eucalyptus Oil, Clove Bud Oil, Potassium Sorbate, Anhydrous Citric Acid.